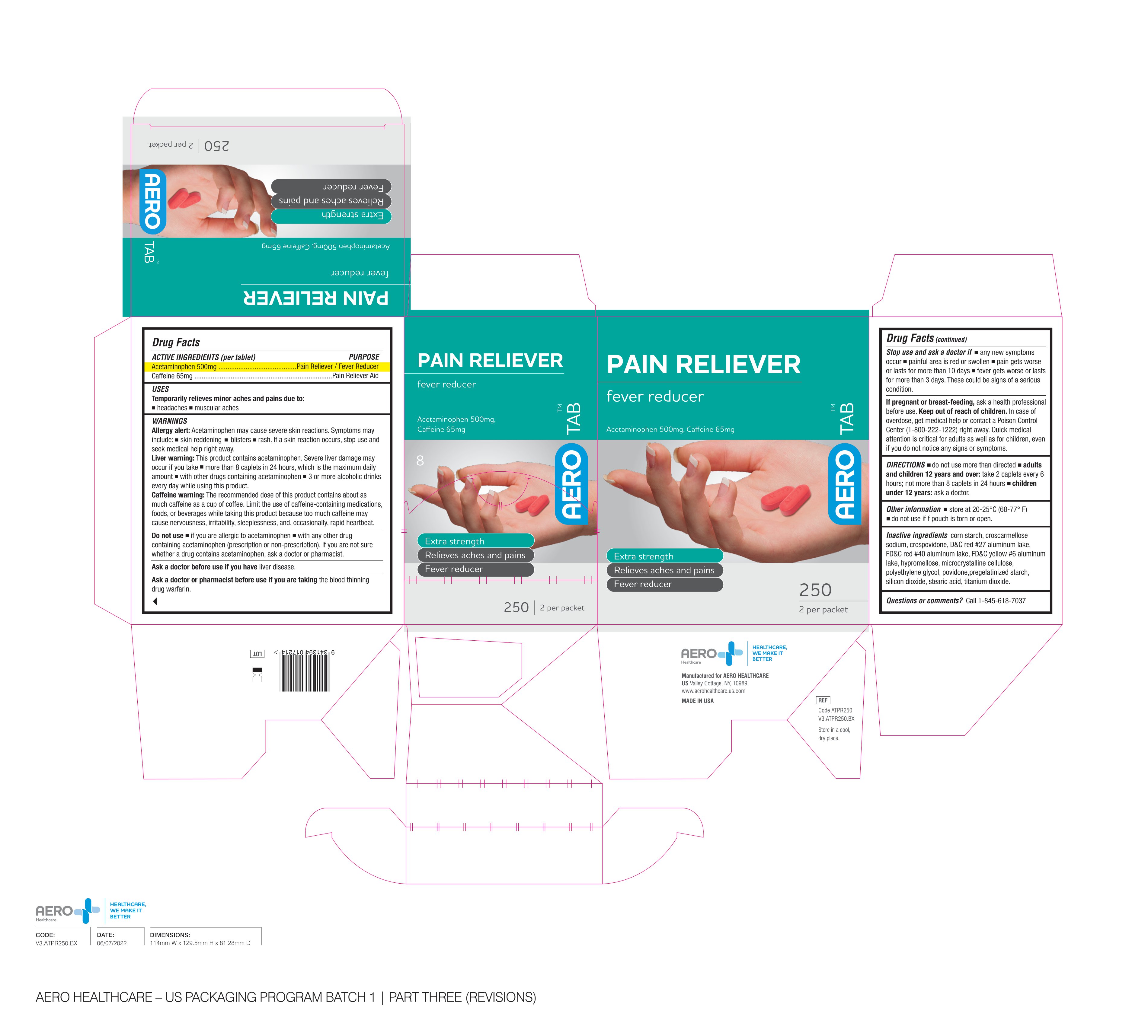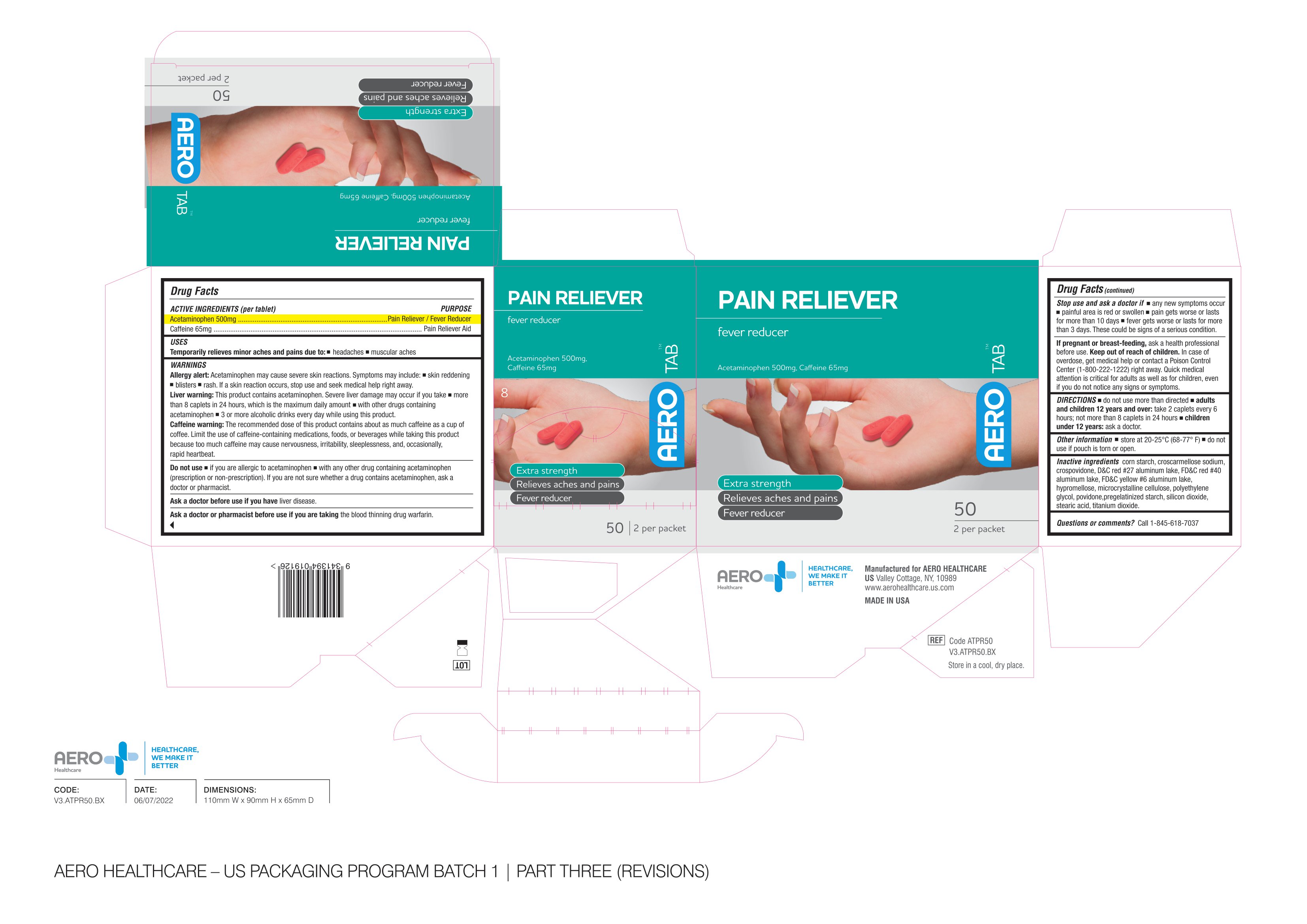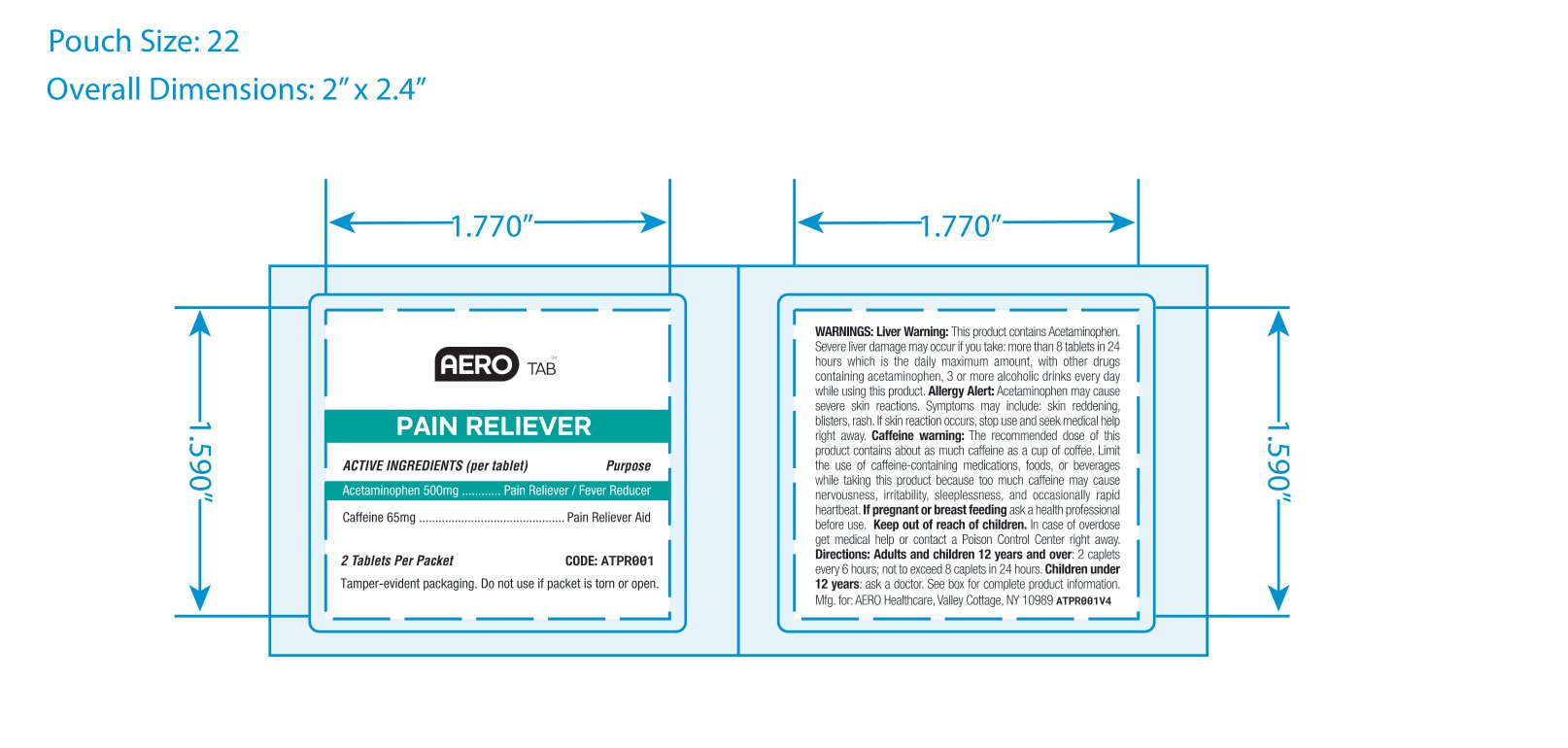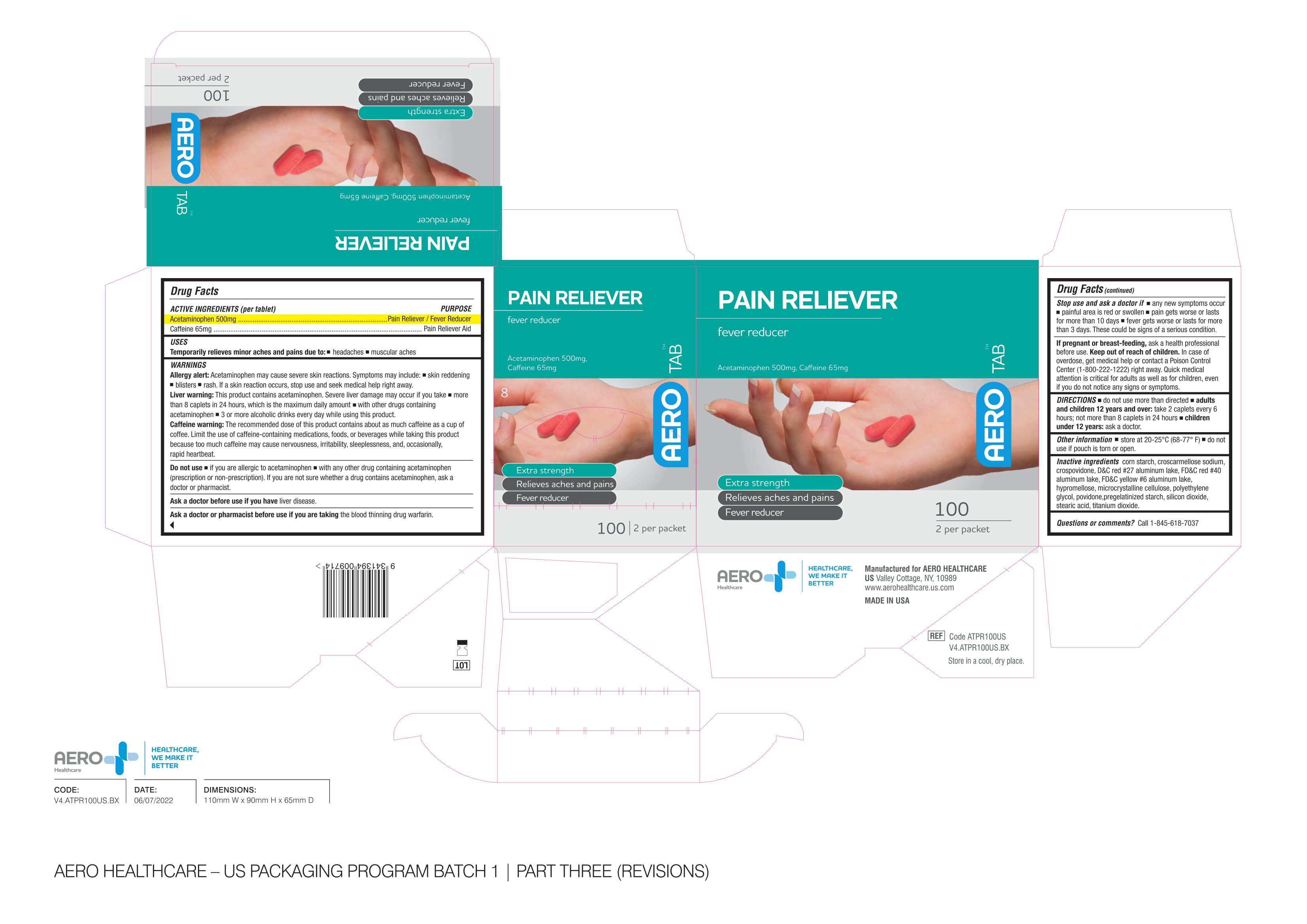 DRUG LABEL: Aerotab Pain Reliever
NDC: 55305-127 | Form: TABLET
Manufacturer: Aero Healthcare
Category: otc | Type: HUMAN OTC DRUG LABEL
Date: 20230306

ACTIVE INGREDIENTS: ACETAMINOPHEN 500 mg/1 1; CAFFEINE 65 mg/1 1
INACTIVE INGREDIENTS: CROSPOVIDONE; FD&C RED NO. 40; HYPROMELLOSE, UNSPECIFIED; MICROCRYSTALLINE CELLULOSE; POLYETHYLENE GLYCOL, UNSPECIFIED; POVIDONE; STEARIC ACID; TITANIUM DIOXIDE; D&C RED NO. 27 ALUMINUM LAKE; FD&C YELLOW NO. 6; SILICON DIOXIDE; STARCH, CORN; CROSCARMELLOSE SODIUM

AEROTAB Pain Reliever

ACTIVE INGREDIENT

Drug Facts

Active Ingredients (per tablet)

Acetaminophen 500mg

Caffeine 65mg

PURPOSE

Acetaminophen 500mg.............Pain Reliever / Fever Reducer

Caffeine 65mg...........................Pain Reliever Aid

USES

Temporarily relieves minor aches and pains due to:

- headaches
- muscular aches

WARNINGS

Allergy Alert: Acetaminophen may cause severe skin reactions. Symptoms may include:

- skin reddening
- blisters
- rash

If a skin reaction occurs, stop use and seek medical help right away.

Liver warning: This product contains acetaminophen. Severe liver damage may occur if you take

- more than 8 caplets in 24 hours, which is the maximum daily amount
- with other drugs containing acetaminophen
- 3 or more alcoholic drinks every day while using this product

Caffeine warning: The recommended dose of this product contains about as much caffeine as a cup of coffee. Limit the use of caffeine-containing medications, foods, or beverages while taking this product because too much caffeine may cause nervousness, irritability, sleeplessness, and occasionaly, rapid heartbeat.

Do not use

- if you are allergic to ascetaminophen
- with any other drug containing acetaminophen (prescription or non-prescription). If you are not sure wheter a drug contains acetaminophen, ask a doctor or pharmacist.

Ask a doctor before use if you have liver disease.

Ask a doctor or pharmacist before use if you are taking the blood thinning drug warfarin.

Stop use and ask a doctor if

- any new symptoms occur
- painful area is red or swollen
- pain gets worse or lasts form ore than 10 days
- fever gets worse or lasts for more than 3 days.

These could be signs of a serious condition.

PREGNANCY OR BREAST FEEDING

If pregnant or breast-feeding, ask a health professional before use.

Keep out of reach of children. In case of overdose, get medical help or contact a Poison Control Center (1-800-222-1222) right away. Quick medical attention is critical for adults as well as for children, even if you do not notice any signs or symptoms.

DIRECTIONS

- do not use more than directed
- adults and children 12 years and over: take 2 caplets every 6 hours; not more than 8 caplets in 24 hours
- children under 12 years: ask a doctor

Other Information

- Store at 20-25 C (68-77 F)
- do not use of pouch is torn or open

Inactive Ingredients

corn starch, croscarmellose sodium, crospovidone, D&C red #27 aluminum lake, FD&C red #40 aluminum lake, FD&C yellow #6 aluminum lake, hypromellose, microcrystalline cellulose, polyethylene glycol, povidone, pregelatinized starch, silicon dioxide, stearic acid, titanium dioxide.

Questions or comments?

Call 1-845-618-7037

PACKAGE LABEL

AEROTAB

Pain Reliever

fever reducer

Acetaminophen 500mg

Caffeine 65mg

Extra Strength

Relieves aches and pains

Fever reducer

2 per packet